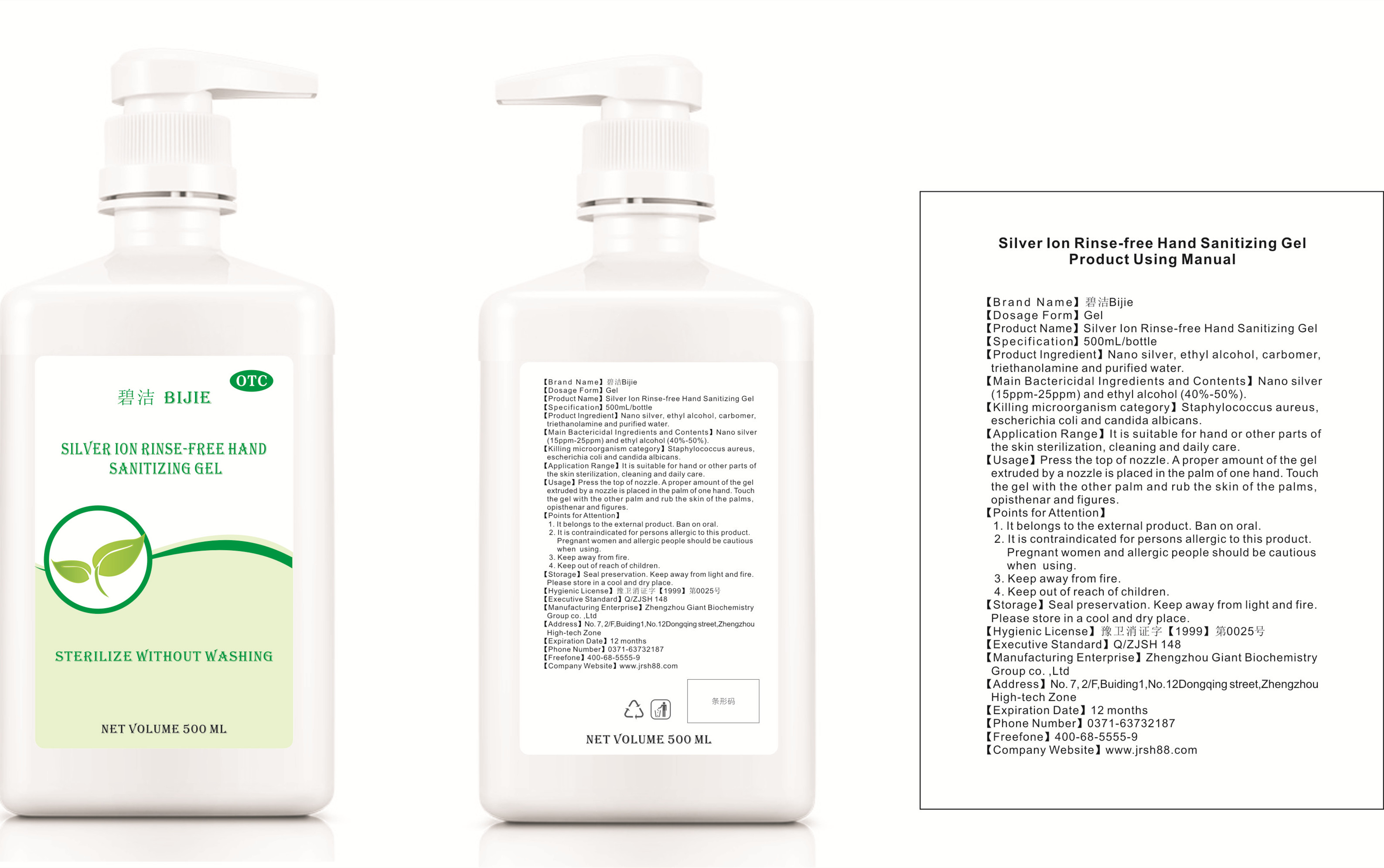 DRUG LABEL: Silver Ion Rinse-free Hand Sanitizing Gel
NDC: 52784-002 | Form: GEL
Manufacturer: ZHENGZHOU GIANT BIOCHEMISTRY GROUP CO., LTD.
Category: otc | Type: HUMAN OTC DRUG LABEL
Date: 20200419

ACTIVE INGREDIENTS: ALCOHOL 187.5 mL/500 mL; SILVER 0.01 mg/500 mL
INACTIVE INGREDIENTS: CARBOMER HOMOPOLYMER, UNSPECIFIED TYPE; WATER; TROLAMINE

DOSAGE AND ADMINISTRATION

Seal preservation. Keep away from light and fire.Please store in a cool and dry place.

INACTIVE INGREDIENT

carbomer,

triethanolamine

purified water.

INDICATIONS AND USAGE

Press the top of nozzle. A proper amount of the gel extruded by a nozzle is placed in the palm of one hand. Touch the gel with the other palm and rub the skin of the palms,opisthenar and figures.

ACTIVE INGREDIENT

Nano silver and ethyl alcohol .

keep out of children

PURPOSE

Disinfection
Sterilization
No Rinseing

WARNINGS

1. It belongs to the external product. Ban on oral.
2. It is contraindicated for persons allergic to this product.Pregnant women and allergic people should be cautious when using.
3. Keep away from fire.
4. Keep out of reach of children.